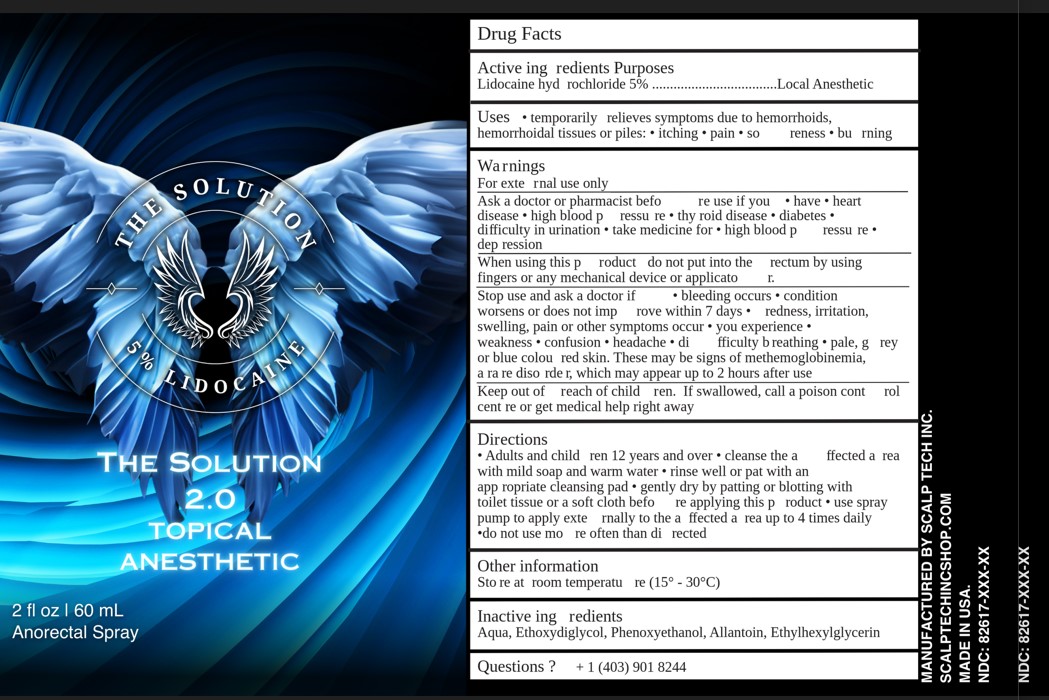 DRUG LABEL: THE SOLUTION 2.0
NDC: 82617-102 | Form: SPRAY
Manufacturer: SCALP TECH INC
Category: otc | Type: HUMAN OTC DRUG LABEL
Date: 20260109

ACTIVE INGREDIENTS: LIDOCAINE HYDROCHLORIDE 5 g/100 mL
INACTIVE INGREDIENTS: DIETHYLENE GLYCOL MONOETHYL ETHER; WATER; PHENOXYETHANOL; ALLANTOIN; ETHYLHEXYLGLYCERIN

SCALP TECH (as PLD) - THE SOLUTION 2.0 (82617-102)

ACTIVE INGREDIENT

LIDOCAINE HCL 5%

PURPOSE

LOCAL ANESTHETIC

USES

TEMPORARILY RELIEVES SYMPTOMS DUE TO HEMORRHOIDS, HEMORRHOIDAL TISSUES OR PILES:

- ITCHING
- PAIN
- SORENESS
- BURNING

WARNINGS

FOR EXTERNAL USE ONLY.

ASK A DOCTOR OR PHARMACIST BEFORE USE IF YOU HAVE

- HEART DISEASE
- HIGH BLOOD PLESSURE
- THYROID DISEASE
- DIABETES
- DIFFICULTY IN URINATION
- TAKE MEDICINE FOR
- HIGH BLOOD PRESSURE
- DEPRESSION

WHEN USING THIS PRODUCT DO NOT PUT INTO THE RECTUM BY USING FINGERS OR ANY MECHANICAL DEVICE OR APPLICATOR.

STOP USE AND ASK A DOCTOR IF

- BLEEDING OCCURS
- CONDITION WORSENS OR DOES NOT IMPROVE WITHIN 7 DAYS
- REDNESS, IRRITATION, SWELLING, PAIN OR OTHER SYMPTOMS OCCUR
- YOU EXPERIENCE
- WEAKNESS
- CONFUSION
- HEADACHE
- DIFFICULTY BREATHING
- PALE, GREY OR BLUE COLOURED SKIN.

tHESE MIGHT BE SIGNS OF METHEMOGLOBINEMIA, A RARE DISORDER, WHICH MAY APPEAR UP TO 2 HOURS AFTER USE.

KEEP OUT OF REACH OF CHILDREN. IF SWALLOWED, CALL A POISON CONTROL CENTER OR GET MEDICAL HELP RIGHT AWAY.

DIRECTIONS

ADULTS AND CHILDREN 12 YEARS AND OVER

- CLEANSE THE AFFECTED AREA WITH MILD SOAP AND WARM WATER
- RINSE WELL OR PAT WITH AN APPROPRIATE CLEANSING PAD
- GENTLY DRY BY PATTING OR BLOTTING WITH TOILET TISSUE OR A SOFT CLOTH BEFORE APPLYING THIS PRODUCT
- USE SPRAY PUMP TO APPLY EXTERNALLY TO THE AFFECTED AREA UP TO 4 TIMES DAILY
- DO NOT USE MORE OFTEN THAN DIRECTED

OTHER INFORMATION

- STORE AT ROOM TEMPERATURE (15° - 30°C)

INACTIVE INGREDIENTS

AQUA, ETHOXYDIGLYCOL, PHENOXYETHANOL, ALLANTOIN, ETHYLHEXYLGLYCERIN

QUESTIONS?

+1 (403) 901 8244